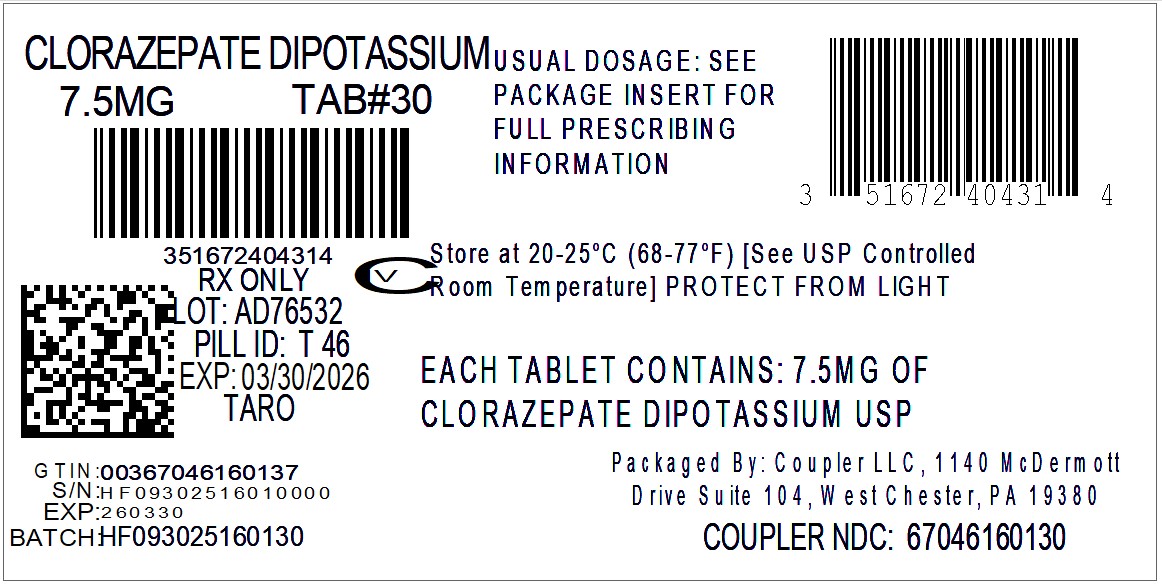 DRUG LABEL: Clorazepate Dipotassium
NDC: 67046-1601 | Form: TABLET
Manufacturer: Coupler LLC
Category: prescription | Type: HUMAN PRESCRIPTION DRUG LABEL
Date: 20250930
DEA Schedule: CIV

ACTIVE INGREDIENTS: CLORAZEPATE DIPOTASSIUM 7.5 mg/1 1
INACTIVE INGREDIENTS: SILICON DIOXIDE; MAGNESIUM OXIDE; MAGNESIUM STEARATE; MICROCRYSTALLINE CELLULOSE; POTASSIUM CARBONATE; POTASSIUM CHLORIDE; TALC; D&C RED NO. 6 BARIUM LAKE; D&C YELLOW NO. 10

Clorazepate Dipotassium Tablets USP, 3.75 mg, 7.5 mg, & 15 mg

CIV

Rx only

WARNING: RISKS FROM CONCOMITANT USE WITH OPIOIDS; ABUSE, MISUSE, AND ADDICTION; and DEPENDENCE AND WITHDRAWAL REACTIONS

- Concomitant use of benzodiazepines and opioids may result in profound sedation, respiratory depression, coma, and death. Reserve concomitant prescribing of these drugs in patients for whom alternative treatment options are inadequate. Limit dosages and durations to the minimum required. Follow patients for signs and symptoms of respiratory depression and sedation (see WARNINGSand PRECAUTIONS).
- The use of benzodiazepines, including clorazepate dipotassium, exposes users to risks of abuse, misuse, and addiction, which can lead to overdose or death. Abuse and misuse of benzodiazepines commonly involve concomitant use of other medications, alcohol, and/or illicit substances, which is associated with an increased frequency of serious adverse outcomes. Before prescribing clorazepate dipotassium and throughout out treatment, assess each patient's risk for abuse, misuse, and addiction (see WARNINGS).
- The continued use of benzodiazepines, including clorazepate dipotassium, may lead to clinically significant physical dependence. The risks of dependence and withdrawal increase with longer treatment duration and higher daily dose. Abrupt discontinuation or rapid dosage reduction of clorazepate dipotassium after continued use may precipitate acute withdrawal reactions, which can be life-threatening. To reduce the risk of withdrawal reactions, use a gradual taper to discontinue clorazepate dipotassium or reduce the dosage (see DOSAGE AND ADMINISTRATIONand WARNINGS).

DESCRIPTION

Chemically, clorazepate dipotassium USP is a benzodiazepine. The empirical formula is C16H11ClK2N2O4; the molecular weight is 408.92; 1 H-1, 4-Benzodiazepine-3-carboxylic acid, 7-chloro-2,3-dihydro-2-oxo-5-phenyl-, potassium salt compound with potassium hydroxide (1:1) and the structural formula may be represented as follows:

The compound occurs as a fine, light yellow, practically odorless powder. It is insoluble in the common organic solvents, but very soluble in water. Aqueous solutions are unstable, clear, light yellow, and alkaline.

Clorazepate dipotassium tablets USP contain 3.75 mg, 7.5 mg or 15 mg of clorazepate dipotassium USP. In addition, each tablet contains the following inactive ingredients: colloidal silicon dioxide, magnesium oxide heavy, magnesium stearate, microcrystalline cellulose, potassium carbonate anhydrous, potassium chloride, talc and the following coloring agents:

3.75 mg - FD&C Blue No. 2 Lake and FD&C Red No. 40 Lake

7.5 mg - D&C Red No. 6 Barium Lake and D&C Yellow No. 10 Lake

15 mg - D&C Red No. 6 Barium Lake and FD&C Red No. 40 Lake

CLINICAL PHARMACOLOGY

Pharmacologically, clorazepate dipotassium has the characteristics of the benzodiazepines. It has depressant effects on the central nervous system. The primary metabolite, nordiazepam, quickly appears in the blood stream. The serum half-life is about 2 days. The drug is metabolized in the liver and excreted primarily in the urine.

Studies in healthy men have shown that clorazepate dipotassium has depressant effects on the central nervous system. Prolonged administration of single daily doses as high as 120 mg was without toxic effects. Abrupt cessation of high doses was followed in some patients by nervousness, insomnia, irritability, diarrhea, muscle aches, or memory impairment.

Since orally administered clorazepate dipotassium is rapidly decarboxylated to form nordiazepam, there is essentially no circulating parent drug. Nordiazepam, the primary metabolite, quickly appears in the blood and is eliminated from the plasma with an apparent half-life of about 40 to 50 hours. Plasma levels of nordiazepam increase proportionally with clorazepate dipotassium dose and show moderate accumulation with repeated administration. The protein binding of nordiazepam in plasma is high (97 to 98%).

Within 10 days after oral administration of a 15 mg (50 μCi) dose of^14C-clorazepate dipotassium to two volunteers, 62 to 67% of the radioactivity was excreted in the urine and 15 to 19% was eliminated in the feces. Both subjects were still excreting measurable amounts of radioactivity in the urine (about 1% of the^14C-dose) on day ten.

Nordiazepam is further metabolized by hydroxylation. The major urinary metabolite is conjugated oxazepam (3-hydroxynordiazepam), and smaller amounts of conjugated p-hydroxynordiazepam and nordiazepam are also found in the urine.

INDICATIONS AND USAGE

Clorazepate dipotassium is indicated for the management of anxiety disorders or for the short-term relief of the symptoms of anxiety. Anxiety or tension associated with the stress of everyday life usually does not require treatment with an anxiolytic.

Clorazepate dipotassium tablets are indicated as adjunctive therapy in the management of partial seizures.

The effectiveness of clorazepate dipotassium tablets in long-term management of anxiety, that is, more than 4 months, has not been assessed by systematic clinical studies. Long-term studies in epileptic patients, however, have shown continued therapeutic activity. The physician should reassess periodically the usefulness of the drug for the individual patient.

Clorazepate dipotassium tablets are indicated for the symptomatic relief of acute alcohol withdrawal.

CONTRAINDICATIONS

Clorazepate dipotassium tablets are contraindicated in patients with a known hypersensitivity to the drug and in those with acute narrow angle glaucoma.

WARNINGS

Risks from Concomitant Use with Opioids

Concomitant use of benzodiazepines, including clorazepate dipotassium, and opioids may result in profound sedation, respiratory depression, coma, and death. Because of these risks, reserve concomitant prescribing of these drugs in patients for whom alternative treatment options are inadequate.

Observational studies have demonstrated that concomitant use of opioid analgesics and benzodiazepines increases the risk of drug-related mortality compared to use of opioids alone. If a decision is made to prescribe clorazepate dipotassium concomitantly with opioids, prescribe the lowest effective dosages and minimum durations of concomitant use, and follow patients closely for signs and symptoms of respiratory depression and sedation. In patients already receiving an opioid analgesic, prescribe a lower initial dose of clorazepate dipotassium than indicated in the absence of an opioid and titrate based on clinical response. If an opioid is initiated in a patient already taking clorazepate dipotassium, prescribe a lower initial dose of the opioid and titrate based upon clinical response.

Advise both patients and caregivers about the risks of respiratory depression and sedation when clorazepate dipotassium is used with opioids. Advise patients not to drive or operate heavy machinery until the effects of concomitant use with the opioid have been determined (see PRECAUTIONS: Drug Interactions).

Abuse, Misuse, and Addiction

The use of benzodiazepines, including clorazepate dipotassium, exposes users to the risks of abuse, misuse, and addiction, which can lead to overdose or death. Abuse and misuse of benzodiazepines often (but not always) involve the use of doses greater than the maximum recommended dosage and commonly involve concomitant use of other medications, alcohol, and/or illicit substances, which is associated with an increased frequency of serious adverse outcomes, including respiratory depression, overdose, or death (see DRUG ABUSE AND DEPENDENCE: Abuse).

Before prescribing clorazepate dipotassium and throughout treatment, assess each patient's risk for abuse, misuse, and addiction (e.g., using a standardized screening tool). Use of clorazepate dipotassium, particularly in patients at elevated risk, necessitates counseling about the risks and proper use of clorazepate dipotassium along with monitoring for signs and symptoms of abuse, misuse, and addiction. Prescribe the lowest effective dosage; avoid or minimize concomitant use of CNS depressants and other substances associated with abuse, misuse, and addiction (e.g., opioid analgesics, stimulants); and advise patients on the proper disposal of unused drug. If a substance use disorder is suspected, evaluate the patient and institute (or refer them for) early treatment, as appropriate.

Dependence and Withdrawal Reactions

To reduce the risk of withdrawal reactions, use a gradual taper to discontinue clorazepate dipotassium or reduce the dosage (a patient-specific plan should be used to taper the dose) (see DOSAGE AND ADMINISTRATION: Discontinuation of Dosage Reduction of Clorazepate Dipotassium).

Patients at an increased risk of withdrawal adverse reactions after benzodiazepine discontinuation or rapid dosage reduction include those who take higher dosages, and those who have had longer durations of use.

Acute Withdrawal Reactions

The continued use of benzodiazepines, including clorazepate dipotassium, may lead to clinically significant physical dependence. Abrupt discontinuation or rapid dosage reduction of clorazepate dipotassium after continued use, or administration of flumazenil (a benzodiazepine antagonist) may precipitate acute withdrawal reactions, which can be life-threatening (e.g., seizures) (see DRUG ABUSE AND DEPENDENCE: Dependence).

Protracted Withdrawal Syndrome

In some cases, benzodiazepine users have developed a protracted withdrawal syndrome with withdrawal symptoms lasting weeks to more than 12 months (see DRUG ABUSE AND DEPENDENCE).

Use in Depressive Neuroses or Psychotic Reactions

Clorazepate dipotassium tablets are not recommended for use in depressive neuroses or in psychotic reactions.

Use in Children

Because of the lack of sufficient clinical experience, clorazepate dipotassium tablets are not recommended for use in patients less than 9 years of age.

Interference with Psychomotor Performance

Patients taking clorazepate dipotassium tablets should be cautioned against engaging in hazardous occupations requiring mental alertness, such as operating dangerous machinery including motor vehicles.

Concomitant Use with CNS Depressants

Since clorazepate dipotassium has a central nervous system depressant effect, patients should be advised against the simultaneous use of other CNS depressant drugs, and cautioned that the effects of alcohol may be increased.

Suicidal Behavior and Ideation

Antiepileptic drugs (AEDs), including clorazepate dipotassium, increase the risk of suicidal thoughts or behavior in patients taking these drugs for any indication. Patients treated with any AED for any indication should be monitored for the emergence or worsening of depression, suicidal thoughts or behavior, and/or any unusual changes in mood or behavior.

Pooled analyses of 199 placebo-controlled clinical trials (mono- and adjunctive therapy) of 11 different AEDs showed that patients randomized to one of the AEDs had approximately twice the risk (adjusted Relative Risk 1.8, 95% CI:1.2, 2.7) of suicidal thinking or behavior compared to patients randomized to placebo. In these trials, which had a median treatment duration of 12 weeks, the estimated incidence rate of suicidal behavior or ideation among 27,863 AED-treated patients was 0.43%, compared to 0.24% among 16,029 placebo-treated patients, representing an increase of approximately one case of suicidal thinking or behavior for every 530 patients treated. There were four suicides in drug-treated patients in the trials and none in placebo-treated patients, but the number is too small to allow any conclusion about drug effect on suicide.

The increased risk of suicidal thoughts or behavior with AEDs was observed as early as one week after starting drug treatment with AEDs and persisted for the duration of treatment assessed. Because most trials included in the analysis did not extend beyond 24 weeks, the risk of suicidal thoughts or behavior beyond 24 weeks could not be assessed.

The risk of suicidal thoughts or behavior was generally consistent among drugs in the data analyzed. The finding of increased risk with AEDs of varying mechanisms of action and across a range of indications suggests that the risk applies to all AEDs used for any indication. The risk did not vary substantially by age (5 to 100 years) in the clinical trials analyzed. Table 1 shows absolute and relative risk by indication for all evaluated AEDs.

Table 1: Risk by indication for antiepileptic drugs in the pooled analysis
Indication | Placebo Patients with Events Per 1000 Patients | Drug Patients with Events Per 1000 Patients | Relative Risk: Incidence of Events in Drug Patients/Incidence in Placebo Patients | Risk Difference: Additional Drug Patients with Events Per 1000 Patients
Epilepsy | 1.0 | 3.4 | 3.5 | 2.4
Psychiatric | 5.7 | 8.5 | 1.5 | 2.9
Other | 1.0 | 1.8 | 1.9 | 0.9
Total | 2.4 | 4.3 | 1.8 | 1.9

The relative risk for suicidal thoughts or behavior was higher in clinical trials for epilepsy than in clinical trials for psychiatric or other conditions, but the absolute risk differences were similar for the epilepsy and psychiatric indications.

Anyone considering prescribing clorazepate dipotassium tablets or any other AED must balance the risk of suicidal thoughts or behavior with the risk of untreated illness. Epilepsy and many other illnesses for which AEDs are prescribed are themselves associated with morbidity and mortality and an increased risk of suicidal thoughts and behavior. Should suicidal thoughts and behavior emerge during treatment, the prescriber needs to consider whether the emergence of these symptoms in any given patient may be related to the illness being treated.

Patients, their caregivers, and families should be informed that AEDs increase the risk of suicidal thoughts and behavior and should be advised of the need to be alert for the emergence or worsening of the signs and symptoms of depression, any unusual changes in mood or behavior, or the emergence of suicidal thoughts, behavior, or thoughts about self-harm. Behaviors of concern should be reported immediately to healthcare providers.

Neonatal Sedation and Withdrawal Syndrome

Use of clorazepate dipotassium late in pregnancy can result in sedation (respiratory depression, lethargy, hypotonia) and/or withdrawal symptoms (hyperreflexia, irritability, restlessness, tremors, inconsolable crying, and feeding difficulties) in the neonate (see PRECAUTIONS: Pregnancy). Monitor neonates exposed to clorazepate dipotassium during pregnancy or labor for signs of sedation and monitor neonates exposed to clorazepate dipotassium during pregnancy for signs of withdrawal; manage these neonates accordingly.

PRECAUTIONS

In those patients in which a degree of depression accompanies the anxiety, suicidal tendencies may be present and protective measures may be required. The least amount of drug that is feasible should be available to the patient.

Patients taking clorazepate dipotassium tablets for prolonged periods should have blood counts and liver function tests periodically. The usual precautions in treating patients with impaired renal or hepatic function should also be observed.

In elderly or debilitated patients, the initial dose should be small, and increments should be made gradually, in accordance with the response of the patient, to preclude ataxia or excessive sedation.

Information for Patients

Advise the patient to read the FDA-approved patient labeling (Medication Guide).

Risks from Concomitant Use with Opioids

Advise both patients and caregivers about the risks of potentially fatal respiratory depression and sedation when clorazepate dipotassium is used with opioids and not to use such drugs concomitantly unless supervised by a health care provider. Advise patients not to drive or operate heavy machinery until the effects of concomitant use with the opioid have been determined (see WARNINGS, Risks from Concomitant Use with Opioidsand PRECAUTIONS, Drug Interactions).

Abuse, Misuse, and Addiction

Inform patients that the use of clorazepate dipotassium, even at recommended dosages, exposes users to risks of abuse, misuse, and addiction, which can lead to overdose and death, especially when used in combination with other medications (e.g., opioid analgesics), alcohol, and/or illicit substances. Inform patients about the signs and symptoms of benzodiazepine abuse, misuse, and addiction; to seek medical help if they develop these signs and/or symptoms; and on the proper disposal of unused drug (see WARNINGSand DRUG ABUSE AND DEPENDENCE).

Withdrawal Reactions

Inform patients that the continued use of clorazepate dipotassium may lead to clinically significant physical dependence and that abrupt discontinuation or rapid dosage reduction of clorazepate dipotassium may precipitate acute withdrawal reactions, which can be life-threatening. Inform patients that in some cases, patients taking benzodiazepines have developed a protracted withdrawal syndrome with withdrawal symptoms lasting weeks to more than 12 months. Instruct patients that discontinuation or dosage reduction of clorazepate dipotassium may require a slow taper (see WARNINGSand DRUG ABUSE AND DEPENDENCE).

Suicidal Thinking and Behavior

Patients, their caregivers, and families should be counseled that AEDs, including clorazepate dipotassium, may increase the risk of suicidal thoughts and behavior and should be advised of the need to be alert for the emergence or worsening of symptoms of depression, any unusual changes in mood or behavior, or the emergence of suicidal thoughts, behavior, or thoughts about self-harm. Behaviors of concern should be reported immediately to healthcare providers.

Pregnancy

Advise pregnant females that use of clorazepate dipotassium late in pregnancy can result in sedation (respiratory depression, lethargy, hypotonia) and/or withdrawal symptoms (hyperreflexia, irritability, restlessness, tremors, inconsolable crying, and feeding difficulties) in newborns (see Warnings, Neonatal Sedation and Withdrawal Syndromeand Precautions, Pregnancy). Instruct patients to inform their healthcare provider if they are pregnant.

Nursing

Advise patients that breastfeeding is not recommended during treatment with clorazepate dipotassium (see Precautions, Nursing Mothers).

DRUG INTERACTIONS

The concomitant use of benzodiazepines and opioids increases the risk of respiratory depression because of actions at different receptor sites in the CNS that control respiration. Benzodiazepines interact at GABAA sites and opioids interact primarily at mu receptors. When benzodiazepines and opioids are combined, the potential for benzodiazepines to significantly worsen opioid-related respiratory depression exists. Limit dosage and duration of concomitant use of benzodiazepines and opioids, and monitor patients closely for respiratory depression and sedation.

If clorazepate dipotassium is to be combined with other drugs acting on the central nervous system, careful consideration should be given to the pharmacology of the agents to be employed. Animal experience indicates that clorazepate dipotassium prolongs the sleeping time after hexobarbital or after ethyl alcohol, increases the inhibitory effects of chlorpromazine, but does not exhibit monoamine oxidase inhibition. Clinical studies have shown increased sedation with concurrent hypnotic medications. The actions of the benzodiazepines may be potentiated by barbiturates, narcotics, phenothiazines, monoamine oxidase inhibitors or other antidepressants.

If clorazepate dipotassium tablets are used to treat anxiety associated with somatic disease states, careful attention must be paid to possible drug interaction with concomitant medication.

In bioavailability studies with normal subjects, the concurrent administration of antacids at therapeutic levels did not significantly influence the bioavailability of clorazepate dipotassium tablets.

Pregnancy

Risk Summary

Neonates born to mothers using benzodiazepines late in pregnancy have been reported to experience symptoms of sedation and/or neonatal withdrawal (see WARNINGS: Neonatal Sedation and Withdrawal Syndromeand Clinical Considerations). Available data from published observational studies of pregnant women exposed to benzodiazepines do not report a clear association with benzodiazepines and major birth defects (see Data) .

The background risk of major birth defects and miscarriage for the indicated population is unknown. All pregnancies have a background risk of birth defect, loss, or other adverse outcomes. In the U.S. general population, the estimated background risk of major birth defects and miscarriage in clinically recognized pregnancies is 2 to 4% and 15 to 20%, respectively.

Clinical Considerations

Fetal/Neonatal Adverse Reactions

Benzodiazepines cross the placenta and may produce respiratory depression, hypotonia, and sedation in neonates. Monitor neonates exposed to clorazepate dipotassium during pregnancy or labor for signs of sedation, respiratory depression, hypotonia, and feeding problems. Monitor neonates exposed to clorazepate dipotassium during pregnancy for signs of withdrawal. Manage these neonates accordingly (see WARNINGS: Neonatal Sedation and Withdrawal Syndrome).

Data

Human Data

Published data from observational studies on the use of benzodiazepines during pregnancy do not report a clear association with benzodiazepines and major birth defects. Although early studies reported an increased risk of congenital malformations with diazepam and chlordiazepoxide, there was no consistent pattern noted. In addition, the majority of more recent case-control and cohort studies of benzodiazepine use during pregnancy, which were adjusted for confounding exposures to alcohol, tobacco and other medications, have not confirmed these findings.

Animal Data

In animal reproduction studies, oral administration of clorazepate to pregnant rats and rabbits at doses up to 150 and 15 mg/kg, respectively, did not cause fetal toxicities or malformation. However, the sedative effects of high dose clorazepate interfered with the maternal care of the offspring.

Nursing Mothers

Risk Summary

Clorazepate and its active metabolite, nordiazepam, are present in breast milk. There are reports of sedation, poor feeding and poor weight gain in infants exposed to benzodiazepines through breast milk. The effects of clorazepate on milk production are unknown. Because of the potential for serious adverse reactions, including sedation and withdrawal symptoms in infants, advise patients that breastfeeding is not recommended during treatment with clorazepate dipotassium.

Pediatric Use

See WARNINGS.

Geriatric Use

Clinical studies of clorazepate dipotassium were not adequate to determine whether subjects aged 65 and over respond differently than younger subjects. Elderly or debilitated patients may be especially sensitive to the effects of all benzodiazepines, including clorazepate dipotassium. In general, elderly or debilitated patients should be started on lower doses of clorazepate dipotassium and observed closely, reflecting the greater frequency of decreased hepatic, renal, or cardiac function, and concomitant disease or other drug therapy. Dose adjustments should also be made slowly, and with more caution in this patient population (see PRECAUTIONSand DOSAGE AND ADMINISTRATION).

ADVERSE REACTIONS

The side effect most frequently reported was drowsiness. Less commonly reported (in descending order of occurrence) were: dizziness, various gastrointestinal complaints, nervousness, blurred vision, dry mouth, headache, and mental confusion. Other side effects included insomnia, transient skin rashes, fatigue, ataxia, genitourinary complaints, irritability, diplopia, depression, tremor, and slurred speech.

There have been reports of abnormal liver and kidney function tests and of decrease in hematocrit.

Decrease in systolic blood pressure has been observed.

To report SUSPECTED ADVERSE REACTIONS, contact Taro Pharmaceuticals U.S.A., Inc. at 1-866-923-4914 or FDA at 1-800-FDA-1088 or www.fda.gov/medwatch.

DRUG ABUSE AND DEPENDENCE

Controlled Substance

Clorazepate dipotassium tablets contain clorazepate, a Schedule IV controlled substance.

Abuse

Clorazepate dipotassium is a benzodiazepine and a CNS depressant with a potential for abuse and addiction. Abuse is the intentional, non-therapeutic use of a drug, even once, for its desirable psychological or physiological effects. Misuse is the intentional use, for therapeutic purposes, of a drug by an individual in a way other than prescribed by a health care provider or for whom it was not prescribed. Drug addiction is a cluster of behavioral, cognitive, and physiological phenomena that may include a strong desire to take the drug, difficulties in controlling drug use (e.g., continuing drug use despite harmful consequences, giving a higher priority to drug use than other activities and obligations), and possible tolerance or physical dependence. Even taking benzodiazepines as prescribed may put patients at risk for abuse and misuse of their medication. Abuse and misuse of benzodiazepines may lead to addiction.

Abuse and misuse of benzodiazepines often (but not always) involve the use of doses greater than the maximum recommended dosage and commonly involve concomitant use of other medications, alcohol, and/or illicit substances, which is associated with an increased frequency of serious adverse outcomes, including respiratory depression, overdose, or death. Benzodiazepines are often sought by individuals who abuse drugs and other substances, and by individuals with addictive disorders (see WARNINGS: Abuse, Misuse, and Addiction).

The following adverse reactions have occurred with benzodiazepine abuse and/or misuse: abdominal pain, amnesia, anorexia, anxiety, aggression, ataxia, blurred vision, confusion, depression, disinhibition, disorientation, dizziness, euphoria, impaired concentration and memory, indigestion, irritability, muscle pain, slurred speech, tremors, and vertigo.

The following severe adverse reactions have occurred with benzodiazepine abuse and/or misuse: delirium, paranoia, suicidal ideation and behavior, seizures, coma, breathing difficulty, and death. Death is more often associated with polysubstance use (especially benzodiazepines with other CNS depressants such as opioids and alcohol).

Dependence

Physical Dependence

Clorazepate dipotassium may produce physical dependence from continued therapy. Physical dependence is a state that develops as a result of physiological adaptation in response to repeated drug use, manifested by withdrawal signs and symptoms after abrupt discontinuation or a significant dose reduction of a drug. Abrupt discontinuation or rapid dosage reduction of benzodiazepines or administration of flumazenil, a benzodiazepine antagonist, may precipitate acute withdrawal reactions, including seizures, which can be life-threatening. Patients at an increased risk of withdrawal adverse reactions after benzodiazepine discontinuation or rapid dosage reduction include those who take higher dosages (i.e., higher and/or more frequent doses) and those who have had longer durations of use (see WARNINGS: Dependence and Withdrawal Reactions).

To reduce the risk of withdrawal reactions, use a gradual taper to discontinue clorazepate dipotassium or reduce the dosage (see DOSAGE AND ADMINISTRATION: Discontinuation or Dosage Reduction of Clorazepate Dipotassiumand WARNINGS: Dependence and Withdrawal Reactions).

Acute withdrawal signs and symptoms associated with benzodiazepines have included abnormal involuntary movements, anxiety, blurred vision, depersonalization, depression, derealization, dizziness, fatigue, gastrointestinal adverse reactions (e.g., nausea, vomiting, diarrhea, weight loss, decreased appetite), headache, hyperacusis, hypertension, irritability, insomnia, memory impairment, muscle pain and stiffness, panic attacks, photophobia, restlessness, tachycardia, and tremor. More severe acute withdrawal signs and symptoms, including life-threatening reactions, have included catatonia, convulsions, delirium tremens, depression, hallucinations, mania, psychosis, seizures and suicidality.

Protracted withdrawal syndrome associated with benzodiazepines is characterized by anxiety, cognitive impairment, depression, insomnia, formication, motor symptoms (e.g., weakness, tremor, muscle twitches), paresthesia, and tinnitus that persists beyond 4 to 6 weeks after initial benzodiazepine withdrawal. Protracted withdrawal symptoms may last weeks to more than 12 months. As a result, there may be difficulty in differentiating withdrawal symptoms from potential re-emergence or continuation of symptoms for which the benzodiazepine was being used.

Tolerance

Tolerance to clorazepate dipotassium may develop from continued therapy. Tolerance is a physiological state characterized by a reduced response to a drug after repeated administration (i.e., a higher dose of a drug is required to produce the same effect that was once obtained at a lower dose). Tolerance to the therapeutic effect of clorazepate dipotassium may develop; however, little tolerance develops to the amnestic reactions and other cognitive impairments caused by benzodiazepines.

OVERDOSAGE

Overdosage of benzodiazepines is characterized by central nervous system depression ranging from drowsiness to coma. In mild to moderate cases, symptoms can include drowsiness, confusion, dysarthria, lethargy, hypnotic state, diminished reflexes, ataxia, and hypotonia. Rarely, paradoxical or disinhibitory reactions (including agitation, irritability, impulsivity, violent behavior, confusion, restlessness, excitement, and talkativeness) may occur. In severe overdosage cases, patients may develop respiratory depression and coma. Overdosage of benzodiazepines in combination with other CNS depressants (including alcohol and opioids) may be fatal (see WARNINGS: Dependence and Withdrawal Reactions). Markedly abnormal (lowered or elevated) blood pressure, heart rate, or respiratory rate raise the concern that additional drugs and/or alcohol are involved in the overdosage.

In managing benzodiazepine overdosage, employ general supportive measures, including intravenous fluids and airway management. Flumazenil, a specific benzodiazepine receptor antagonist indicated for the complete or partial reversal of the sedative effects of benzodiazepines in the management of benzodiazepine overdosage, can lead to withdrawal and adverse reactions, including seizures, particularly in the context of mixed overdosage with drugs that increase seizure risk (e.g., tricyclic and tetracyclic antidepressants) and in patients with long-term benzodiazepine use and physical dependency. The risk of withdrawal seizures with flumazenil use may be increased in patients with epilepsy. Flumazenil is contraindicated in patients who have received a benzodiazepine for control of a potentially life-threatening condition (e.g., status epilepticus). If the decision is made to use flumazenil, it should be used as an adjunct to, not as a substitute for, supportive management of benzodiazepine overdosage. See the flumazenil injection Prescribing Information.

Consider contacting the Poison Help line (1-800-222-1222) or a medical toxicologist for additional overdosage management recommendations.

DOSAGE AND ADMINISTRATION

For the Symptomatic Relief of Anxiety

Clorazepate dipotassium tablets are administered orally in divided doses. The usual daily dose is 30 mg. The dose should be adjusted gradually within the range of 15 to 60 mg daily in accordance with the response of the patient. In elderly or debilitated patients it is advisable to initiate treatment at a daily dose of 7.5 to 15 mg.

Clorazepate dipotassium tablets may also be administered in a single dose daily at bedtime; the recommended initial dose is 15 mg. After the initial dose, the response of the patient may require adjustment of subsequent dosage. Lower doses may be indicated in the elderly patient. Drowsiness may occur at the initiation of treatment and with dosage increment.

For the Symptomatic Relief of Acute Alcohol Withdrawal

The following dosage schedule is recommended:

1st 24 hours (Day 1) | 30 mg initially; followed by 30 to 60 mg in divided doses
2nd 24 hours (Day 2) | 45 to 90 mg in divided doses
3rd 24 hours (Day 3) | 22.5 to 45 mg in divided doses
Day 4 | 15 to 30 mg in divided doses

Thereafter, gradually reduce the daily dose to 7.5 to 15 mg. Discontinue drug therapy as soon as patient's condition is stable.

The maximum recommended total daily dose is 90 mg. Avoid excessive reductions in the total amount of drug administered on successive days.

As an Adjunct to Antiepileptic Drugs

In order to minimize drowsiness, the recommended initial dosages and dosage increments should not be exceeded.

Adults

The maximum recommended initial dose in patients over 12 years old is 7.5 mg three times a day. Dosage should be increased by no more than 7.5 mg every week and should not exceed 90 mg/day.

Children (9 to 12 years)

The maximum recommended initial dose is 7.5 mg two times a day. Dosage should be increased by no more than 7.5 mg every week and should not exceed 60 mg/day.

Discontinuation or Dosage Reduction of Clorazepate Dipotassium

To reduce the risk of withdrawal reactions, use a gradual taper to discontinue clorazepate dipotassium or reduce the dosage. If a patient develops withdrawal reactions, consider pausing the taper or increasing the dosage to the previous tapered dosage level. Subsequently decrease the dosage more slowly (see WARNINGSand DRUG ABUSE AND DEPENDENCE).

ANIMAL PHARMACOLOGY AND TOXICOLOGY

Studies in rats and monkeys have shown a substantial difference between doses producing tranquilizing, sedative and toxic effects. In rats, conditioned avoidance response was inhibited at an oral dose of 10 mg/kg; sedation was induced at 32 mg/kg; the LD50was 1320 mg/kg. In monkeys aggressive behavior was reduced at an oral dose of 0.25 mg/kg; sedation (ataxia) was induced at 7.5 mg/kg; the LD50could not be determined because of the emetic effect of large doses, but the LD50exceeds 1600 mg/kg.

Twenty-four dogs were given clorazepate dipotassium orally in a 22-month toxicity study; doses up to 75 mg/kg were given. Drug-related changes occurred in the liver; weight was increased and cholestasis with minimal hepatocellular damage was found, but lobular architecture remained well preserved.

Eighteen rhesus monkeys were given oral doses of clorazepate dipotassium from 3 to 36 mg/kg daily for 52 weeks. All treated animals remained similar to control animals.

Although total leucocyte count remained within normal limits it tended to fall in the female animals on the highest doses.

Examination of all organs revealed no alterations attributable to clorazepate dipotassium. There was no damage to liver function or structure.

Reproduction Studies

In fertility studies, clorazepate did not alter the fertility indices or reproductive capacity of adult animals (see Pregnancy).

HOW SUPPLIED

Clorazepate Dipotassium Tablets USP are available as tablets containing 3.75 mg, 7.5 mg or 15 mg of clorazepate dipotassium, USP.

The 3.75 mg tablets are round flat beveled edge, pale violet colored slightly mottled tablet. One side is scored and engraved with "T" above the score and "45" below the score. Other side is plain.

Bottles of 100 (NDC 51672-4042-1)

Bottles of 500 (NDC 51672-4042-2)

Bottles of 1,000 (NDC 51672-4042-3)

The 7.5 mg tablets are round flat beveled edge, orange colored, slightly mottled tablet. One side is scored and engraved with "T" above the score and "46" below the score. Other side is plain. Bottles of 100 (NDC 51672-4043-1)

Bottles of 500 (NDC 51672-4043-2)

Bottles of 1,000 (NDC 51672-4043-3)

The 15 mg tablets are round flat beveled edge, pale pink colored, slightly mottled tablet. One side is scored and engraved with "T" above the score and"47" below the score. Other side is plain.

Bottles of 100 (NDC 51672-4044-1)

Bottles of 500 (NDC 51672-4044-2)

Bottles of 1,000 (NDC 51672-4044-3)

Recommended storage

Protect from moisture. Keep bottle tightly closed. Store at 20° to 25°C (68° to 77°F)[see USP Controlled Room Temperature]. Dispense in a USP tight, light-resistant container.

Manufactured by: Taro Pharmaceutical Industries Ltd.
Haifa Bay, Israel 2624761
Distributed by: Taro Pharmaceuticals U.S.A., Inc.
Hawthorne, NY 10532
Revised: September 2024

5200400-0924-07

MEDICATION GUIDE
CLORAZEPATE DIPOTASSIUM
(klor azʹ e pate dyeʺ poe tasʹ ee um) TABLETS CIV

What is the most important information I should know about clorazepate dipotassium tablets?

- Clorazepate dipotassium tablets is a benzodiazepine medicine. Taking benzodiazepines with opioid medicines, alcohol, or other central nervous system (CNS) depressants (including street drugs) can cause severe drowsiness, breathing problems (respiratory depression), coma and death.Get emergency help right away if any of the following happens:
  - shallow or slowed breathing
  - breathing stops (which may lead to the heart stopping)
  - excessive sleepiness (sedation)
    Do not drive or operate heavy machinery until you know how taking clorazepate dipotassium tablets and opioids affects you.
- Risk of abuse, misuse, and addiction.There is a risk of abuse, misuse, and addiction with benzodiazepines including clorazepate dipotassium tablets which can lead to overdose and serious side effects including coma and death.
  - Serious side effects including coma and death have happened in people who have abused or misused benzodiazepines, including clorazepate dipotassium tablets.These serious side effects may also include delirium, paranoia, suicidal thoughts or actions, seizures, and difficulty breathing. Call your healthcare provider or go to the nearest hospital emergency room right away if you get any of these serious side effects.
  - You can develop an addiction even if you take clorazepate dipotassium tablets as prescribed by your healthcare provider.
  - Take clorazepate dipotassium tablets exactly as your healthcare provider prescribed.
  - Do not share your clorazepate dipotassium tablets with other people.
  - Keep clorazepate dipotassium tablets in a safe place and away from children.
- Physical dependence and withdrawal reactions.Clorazepate dipotassium tablets can cause physical dependence and withdrawal reactions.
  - Do not suddenly stop taking clorazepate dipotassium tablets.Stopping clorazepate dipotassium tablets suddenly can cause serious and life-threatening side effects, including, unusual movements, responses, or expressions, seizures, sudden and severe mental or nervous system changes, depression, seeing or hearing things that others do not see or hear, an extreme increase in activity or talking, losing touch with reality, and suicidal thoughts or actions. Call your healthcare provider or go to the nearest hospital emergency room right away if you get any of these symptoms.
  - Some people who suddenly stop benzodiazepines have symptoms that can last for several weeks to more than 12 months,including, anxiety, trouble remembering, learning, or concentrating, depression, problems sleeping, feeling like insects are crawling under your skin, weakness, shaking, muscle twitching, burning or prickling feeling in your hands, arms, legs or feet, and ringing in your ears.
  - Physical dependence is not the same as drug addiction. Your healthcare provider can tell you more about the differences between physical dependence and drug addiction.
  - Do not take more clorazepate dipotassium tablets than prescribed or take clorazepate dipotassium tablets for longer than prescribed.
- Like other antiepileptic medicines, clorazepate dipotassium may cause suicidal thoughts or actions in a very small number of people, about 1 in 500.

Call your healthcare provider right away if you have any of these symptoms, especially if they are new, worse, or worry you:

- thoughts about suicide or dying
- attempts to commit suicide
- new or worse depression
- new or worse anxiety
- feeling agitated or restless
- panic attacks
- trouble sleeping (insomnia)

- new or worse irritability
- acting aggressive, being angry, or violent
- acting on dangerous impulses
- an extreme increase in activity and talking (mania)
- other unusual changes in behavior or mood

How can I watch for early symptoms of suicidal thoughts and actions?

- Pay attention to any changes, especially sudden changes, in mood, behaviors, thoughts, or feelings.
- Keep all follow-up visits with your healthcare provider as scheduled.

Call your healthcare provider between visits as needed, especially if you are worried about symptoms.

Stopping a seizure medicine suddenly in a patient who has epilepsy can cause seizures that will not stop (status epilepticus).

Suicidal thoughts or actions can be caused by things other than medicines. If you have suicidal thoughts or actions, your healthcare provider may check for other causes.

What is clorazepate dipotassium?
Clorazepate dipotassium is a prescription medicine used:

- to treat anxiety disorders
- with other medicines to treat partial seizures
- to treat the symptoms of sudden alcohol withdrawal

Clorazepate dipotassium tablets is a federally controlled substance (C-IV) because it contains clorazepate dipotassium that can be abused or lead to dependence.Keep clorazepate dipotassium tablets in a safe place to prevent misuse and abuse. Selling or giving away clorazepate dipotassium tablets may harm others, and is against the law. Tell your healthcare provider if you have ever abused or been dependent on alcohol, prescription medicines or street drugs.
It is not known if clorazepate dipotassium is safe and effective in children less than 9 years of age.

Do not take clorazepate dipotassium if you:

- are allergic to clorazepate dipotassium or any of the ingredients in clorazepate dipotassium tablets. See the end of this Medication Guide for a complete list of ingredients in clorazepate dipotassium tablets.

Before you take clorazepate dipotassium, tell your healthcare provider about all your medical conditions, including if you:

- have liver or kidney problems
- have or have had depression, mood problems, or suicidal thoughts or behavior
- have a history of abnormal thinking and behavior (psychotic reactions)
- are pregnant or plan to become pregnant.
  - Taking clorazepate dipotassium late in pregnancy may cause your baby to have symptoms of sedation (breathing problems, sluggishness, low muscle tone), and/or withdrawal symptoms (jitteriness, irritability, restlessness, shaking, excessive crying, feeding problems).
  - Tell your healthcare provider right away if you become pregnant or think you are pregnant during treatment with clorazepate dipotassium.
  - are breastfeeding or plan to breastfeed. Clorazepate dipotassium passes into breast milk.
- Talk to your healthcare provider about the best way to feed your baby if you take clorazepate dipotassium tablets.
- Breastfeeding is not recommended during treatment with clorazepate dipotassium.

Tell your healthcare provider about all the medicines you take,including prescription and over-the-counter medicines, vitamins, and herbal supplements.

Taking clorazepate dipotassium with certain other medicines can cause side effects or affect how well clorazepate dipotassium or the other medicines work. Do not start or stop other medicines without talking to your healthcare provider.

How should I take clorazepate dipotassium tablets?

- Take clorazepate dipotassium tablets exactly as your healthcare provider tells you to take it. Your healthcare provider will tell you how much clorazepate dipotassium to take and when to take it.
- Your healthcare provider may change your dose if needed. Do not change your dose of clorazepate dipotassium tablets without talking to your healthcare provider.
- Do not stop taking clorazepate dipotassium tablets without first talking to your healthcare provider. Stopping clorazepate dipotassium tablets suddenly can cause serious problems.
- If you take too much clorazepate dipotassium tablets, call your healthcare provider or go to the nearest hospital emergency room right away.

What are the possible side effects of clorazepate dipotassium tablets?
Clorazepate dipotassium tablets may cause serious side effects, including: See " What is the most important information I should know about clorazepate dipotassium tablets?"

- Clorazepate dipotassium tablets can make you sleepy or dizzy and can slow your thinking and motor skills.Do not drive, operate heavy machinery, or do other dangerous activities until you know how clorazepate dipotassium tablets affects you.
- Do not drink alcohol or take other drugs that may make you sleepy or dizzy while taking clorazepate dipotassium tablets without first talking to your healthcare provider.When taken with alcohol or drugs that cause sleepiness or dizziness, clorazepate dipotassium tablets may make your sleepiness or dizziness much worse.

The most common side effects of clorazepate dipotassium tablets include:

- drowsiness
- dizziness

- upset stomach
- blurred vision

- dry mouth

These are not all the possible side effects of clorazepate dipotassium. For more information, ask your healthcare provider or pharmacist.

Call your doctor for medical advice about side effects. You may report side effects to FDA at 1-800-FDA-1088.

How should I store clorazepate dipotassium tablets?

- Store clorazepate dipotassium tablets between 68ºF to 77ºF (20ºC to 25ºC).
- Keep clorazepate dipotassium tablets in a tightly closed container, dry, and out of the light.
- Keep clorazepate dipotassium tablets and all medicines out of the reach of children.

General information about the safe and effective use of clorazepate dipotassium tablets.

Medicines are sometimes prescribed for purposes other than those listed in a Medication Guide. Do not use clorazepate dipotassium for a condition for which it was not prescribed. Do not give clorazepate dipotassium to other people, even if they have the same symptoms that you have. It may harm them. You can ask your pharmacist or healthcare provider for information about clorazepate dipotassium that is written for health professionals.

What are the ingredients in clorazepate dipotassium tablets?

Active ingredient:clorazepate dipotassium

Inactive ingredients:colloidal silicon dioxide, magnesium oxide heavy, magnesium stearate, microcrystalline cellulose, potassium carbonate anhydrous, potassium chloride, talc and the following coloring agents:
3.75 mg - FD&C Blue No. 2 Lake and FD&C Red No. 40 Lake
7.5 mg - D&C Red No. 6 Barium Lake and D&C Yellow No. 10 Lake
15 mg - D&C Red No. 6 Barium Lake and FD&C Red No. 40 Lake

For more information about clorazepate dipotassium, go to www.taro.com or call Taro Pharmaceuticals U.S.A., Inc. at 1-866-923-4914.

Manufactured by: Taro Pharmaceutical Industries Ltd., Haifa Bay, Israel 2624761
Distributed by: Taro Pharmaceuticals U.S.A., Inc.,Hawthorne, NY 10532

This Medication Guide has been approved by the U.S. Food and Drug Administration.
Revised: September 2024
5200400-0924-07